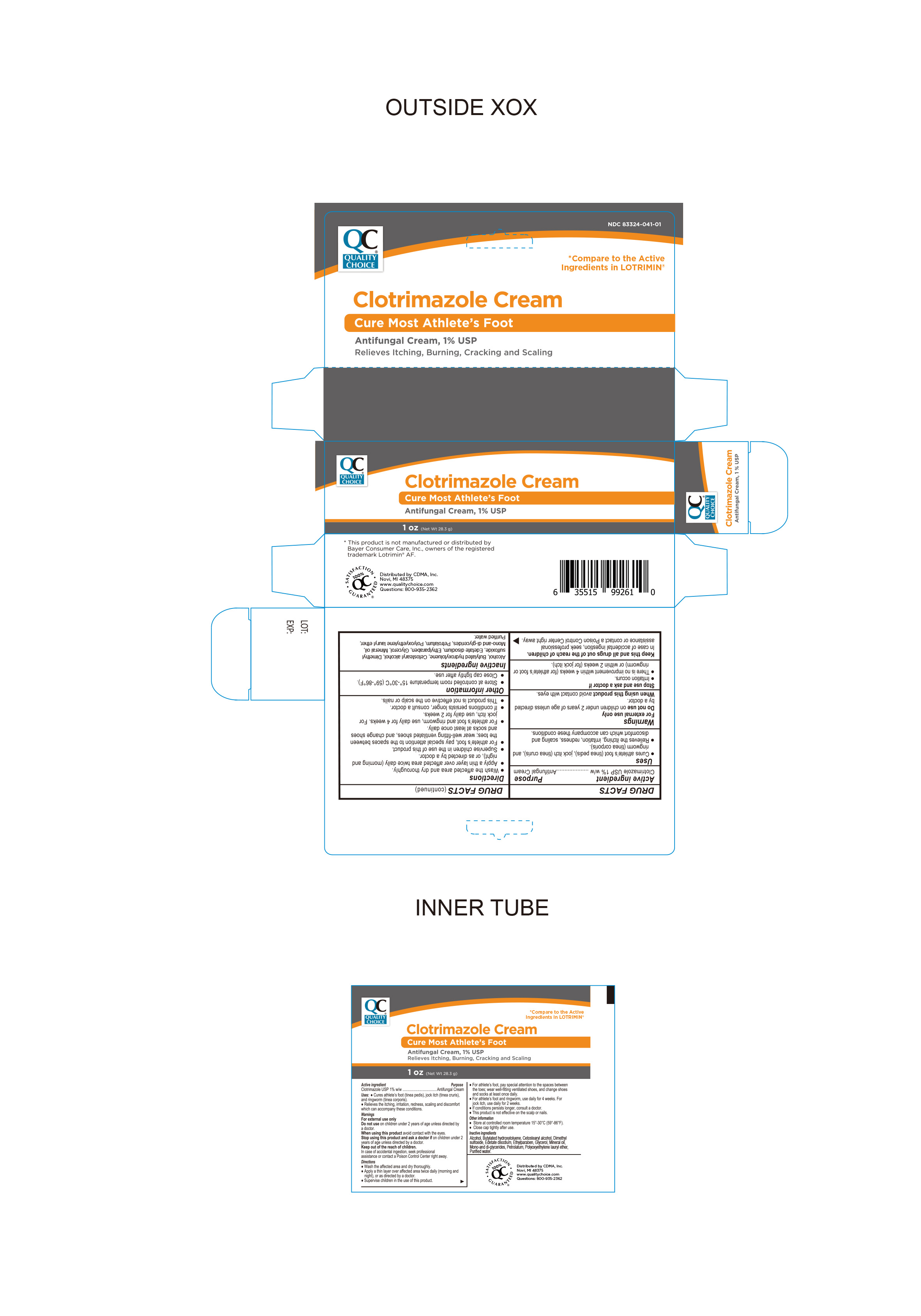 DRUG LABEL: Clotrimazole 1%
NDC: 83324-041 | Form: CREAM
Manufacturer: Chain Drug Marketing Association Inc.
Category: otc | Type: HUMAN OTC DRUG LABEL
Date: 20241021

ACTIVE INGREDIENTS: CLOTRIMAZOLE 1 g/100 g
INACTIVE INGREDIENTS: BUTYLATED HYDROXYTOLUENE; CETOSTEARYL ALCOHOL; GLYCERYL MONO- AND DICAPRYLATE; MINERAL OIL; ALCOHOL; DIMETHYL SULFOXIDE; ETHYLPARABEN; GLYCERIN; LAURETH-23; PETROLATUM; WATER; EDETATE DISODIUM

Quality Choice Clotrimazole cream USP, 1%

Active ingredient

Clotrimazole USP 1% w/w

Purpose

Antifungal Cream

KEEP OUT OF REACH OF CHILDREN

In case of accidental ingestion, seek professional assistance or contact a Poison Control right away.

Uses

Cures athlete’s foot (tinea pedis), jock itch (tinea cruris), ringworm (tinea corporis). Relieves the itching, irritation, redness, scaling and discomfort which can accompany these conditions.

Warnings

For External Use Only

● Do not use on children under 2 years of age unless directed by a doctor.

● When using this product avoid contact with eyes.

Stop Use and ask a Doctor if:

On children under 2 years of age unless directed by doctor.

Directions

- Wash the affected area and dry thoroughly.

● Apply a thin layer of this product over affected area twice daily (morning and night), or as directed by a doctor.

● Supervise children in the use of this product.

● For athlete’s foot, pay special attention to the spaces between the toes; wear well-fitting ventilated shoes, and change shoes and socks at least once daily.

● For athlete’s foot and ringworm, use daily for 4 weeks. For jock itch, use daily for 2 weeks.

● If conditions persists longer, consult a doctor.

● This product is not effective on the scalp or nails.

Inactive Ingredients

Dimethyl Sulfoxide, Ethylparaben, Glycerol, Alcohol, Butylated hydroxytoluene, Cetostearyl alcohol, Edetate disodium, Mineral oil, mono and di glycerides, petrolatum, Polyoxyethylene lauryl ether, purified water.

Other Information

- store at controlled room temperature 15°-30°C (59°- 86°F)
- Close cap tightly after use.

Questions or Comments?

DISTRIBUTED BY: CDMA Inc.

Novi, MI. 48375

www.qualitychoice.com

This product is not manufactured or distributed by Bayer Consumer Care, Inc. owner of the registered trademark Lotrimin® AF